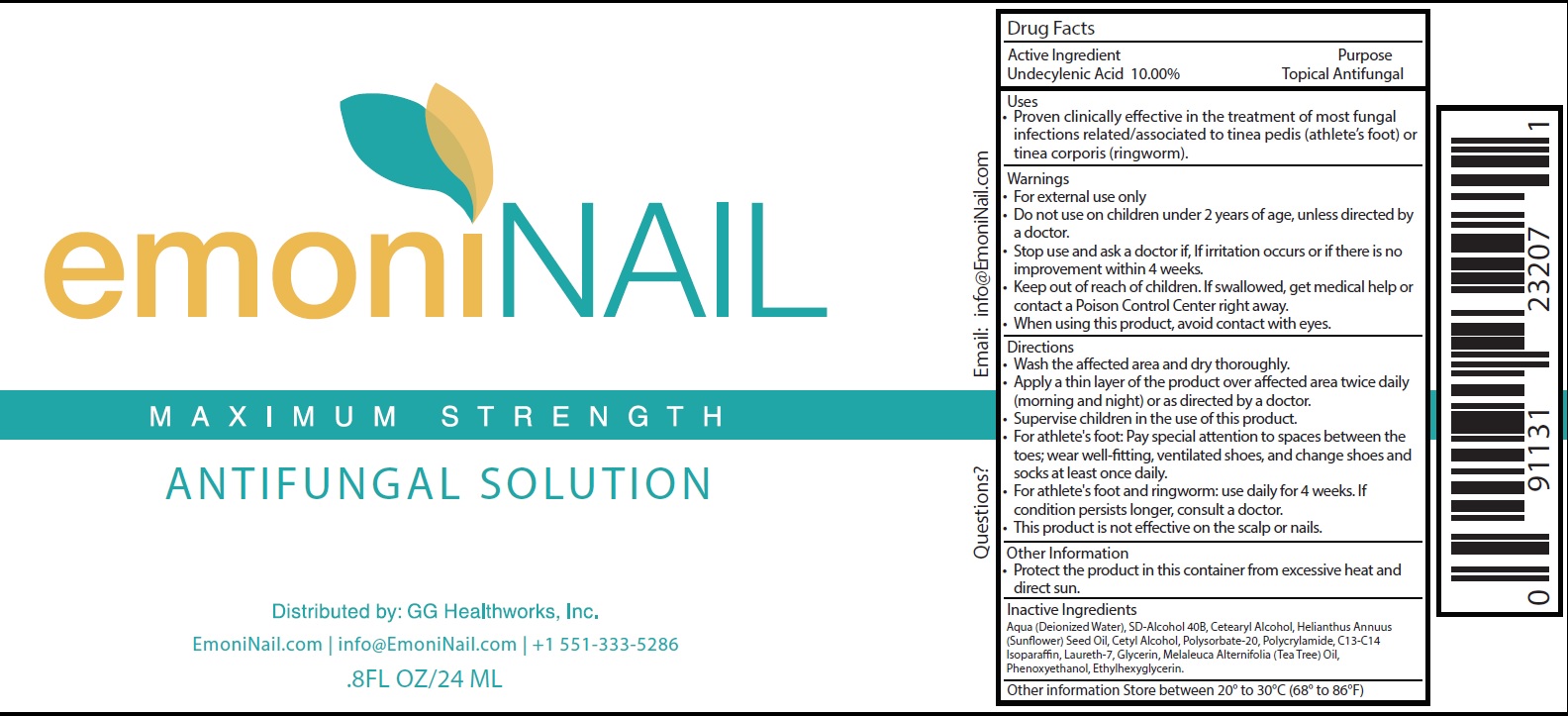 DRUG LABEL: EmoniNail Antifungal
NDC: 76973-071 | Form: LIQUID
Manufacturer: GG Healthworks Inc.
Category: otc | Type: HUMAN OTC DRUG LABEL
Date: 20231106

ACTIVE INGREDIENTS: UNDECYLENIC ACID 100 mg/1 mL
INACTIVE INGREDIENTS: WATER; CETOSTEARYL ALCOHOL; SUNFLOWER OIL; CETYL ALCOHOL; POLYSORBATE 20; C13-14 ISOPARAFFIN; LAURETH-7; GLYCERIN; TEA TREE OIL; PHENOXYETHANOL; ETHYLHEXYLGLYCERIN

EmoniNail Antifungal Solution

Active Ingredient

Undecylenic Acid 10.00%

Purpose

Topical Antifungal

Uses

Proven clinically effective in the treatment of most fungal infections related/associated to tinea pedis (athlete's foot) or tinea corporis (ringworm).

Warnings

- For external use only

Do not use

- on children under 2 years of age, unless directed by a doctor.

Stop use and ask a doctor if,

- If irritation occurs or if there is no improvement within 4 weeks.

Keep out of reach of children.

If swallowed, get medical help or contact a Poison Control Center right away.

When using this product,

avoid contact with eyes.

Directions

- Wash the affected area and dry thoroughly.
- Apply a thin layer of the product over affected area twice daily (morning and night) or as directed by a doctor.
- Supervise children in the use of this product.
- For athlete's foot: Pay special attention to spaces between the toes; wear well-fitting, ventilated shoes, and change shoes andsocks at least once daily.
- For athlete's foot and ringworm: use daily for 4 weeks. If condition persists longer, consult a doctor.
- This product is not effective on the scalp or nails.

Other Information

- Protect the product in this container from excessive heat and direct sun.

Inactive Ingredients

Aqua (Deionized Water), SD-Alcohol 40B, Cetearyl Alcohol, Helianthus Annuus (Sunflower) Seed Oil, Cetyl Alcohol, Polysorbate-20, Polycrylamide, C13-C14 Isoparaffin, Laureth-7, Glycerin, Melaleuca Alternifolia (Tea Tree) Oil, Phenoxyethanol, Ethylhexyglycerin.

Other information

Store between 20° to 30°C (68° to 86°F)